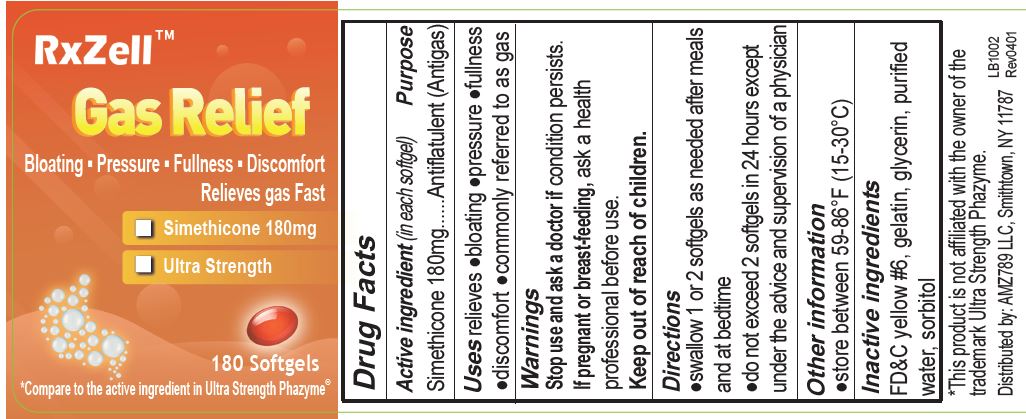 DRUG LABEL: Simethicone
NDC: 73629-002 | Form: CAPSULE, LIQUID FILLED
Manufacturer: AMZ789 LLC
Category: otc | Type: HUMAN OTC DRUG LABEL
Date: 20250108

ACTIVE INGREDIENTS: DIMETHICONE 180 mg/1 1
INACTIVE INGREDIENTS: WATER; GLYCERIN; FD&C YELLOW NO. 6; GELATIN

Simethicone 180mg

ACTIVE INGREDIENT

Simethicone 180mg

PURPOSE

relieves bloating, pressure, fullness, commonly referred to as gas

WARNINGS

stop use and ask a doctor if condition persists

PREGNANCY OR BREAST FEEDING

if pregnant or breast-feedingm ask a health professional before use

Keep out of reach of children

DOSAGE AND ADMINISTRATION

▪ swallow one or two softgels as needed after a meal

▪ do not exceed two softgels per day except under the advice and supervision of a physician

INDICATIONS AND USAGE

Uses relieves ▪ bloating ▪ pressure ▪ fullness commonly referred to as gas

INACTIVE INGREDIENT

FD&C yellow #6, gelatin, glycerin, purified water, sorbitol

PACKAGE LABEL

RxZell

Fast Acting Gas Relief